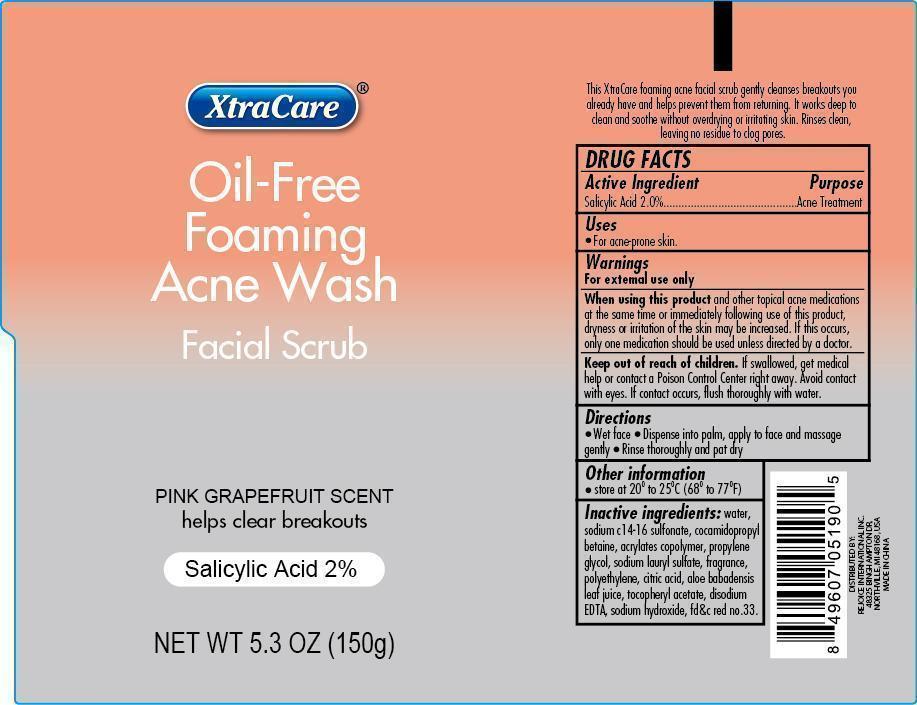 DRUG LABEL: Oil-Free Foaming Acne Wash
NDC: 57337-031 | Form: GEL
Manufacturer: Rejoice International
Category: otc | Type: HUMAN OTC DRUG LABEL
Date: 20251020

ACTIVE INGREDIENTS: SALICYLIC ACID 3 g/150 g
INACTIVE INGREDIENTS: WATER; SODIUM C14-16 OLEFIN SULFONATE; COCAMIDOPROPYL BETAINE; CARBOMER COPOLYMER TYPE A (ALLYL PENTAERYTHRITOL CROSSLINKED); PROPYLENE GLYCOL; SODIUM LAURYL SULFATE; POLYETHYLENE GLYCOL 1000; CITRIC ACID MONOHYDRATE; ALOE VERA LEAF; TOCOPHEROL; EDETATE DISODIUM; SODIUM HYDROXIDE; D&C RED NO. 33

5.3OZ OIL FREE FOAMING FACIAL SCRUB - PINK GRAPE

Active Ingredient Purpose

Salicylic Acid 2%................Acne Treatment

PURPOSE

Oil-Free Foaming Acne Wash Facial Scrub

Pink Grapefruit Scent

helps clear breakouts

Salicylic Acid 2%

Keep out of reach of children. If swallowed, get medical help or contact a Poison Control Center right away. Avoid contact with eyes. If contact occurs, flush thoroughly with water.

INDICATIONS AND USAGE

This XtraCare foaming acne facial scrub gently cleanses breakouts you already have and helps prevent them from returning. It works deep to clean and soothe without overdrying or irritating skin. Rinses clean, leaving no residue to clog pores.

Uses

for acne-prone skin.

Warnings: for external use only.

When using this product and other topical acne medications at the same time or immediately following use of this product, dryness or irritation of the skin may be increased. If this occurse, only one medication should be used unless directed by a doctor.

Directions:

Wet face.

Dispense into palm, apply to face and massage gently.

Rinse thoroughly and pat dry.

INACTIVE INGREDIENT

Inactive Ingredients: water, sodium c14-16 olefin sulfonate, cocamidopropyl betaine, acrylates copolymer, propylene glycol, sodium lauryl sulfate, fragrance, polyethylene glycol, sodium lauryl sulfate, fragrance, polyethylene, citric acid, aloe barbadensis leaf juice, tocopheryl acetate, disodium EDTA, sodium hydroxide, FD&C red no.33

Other Information

store at 20oC to 25oC (68o to 77oF)